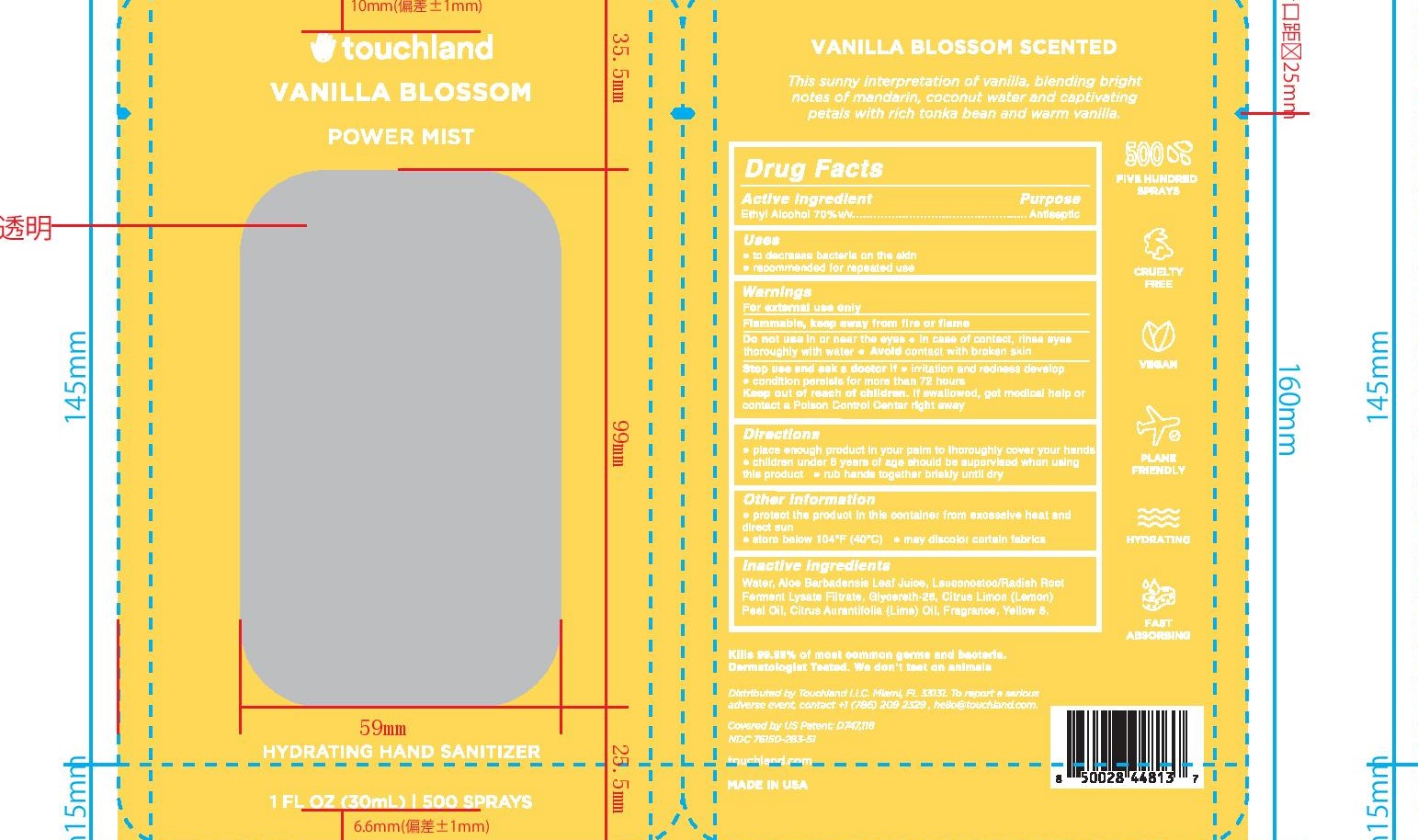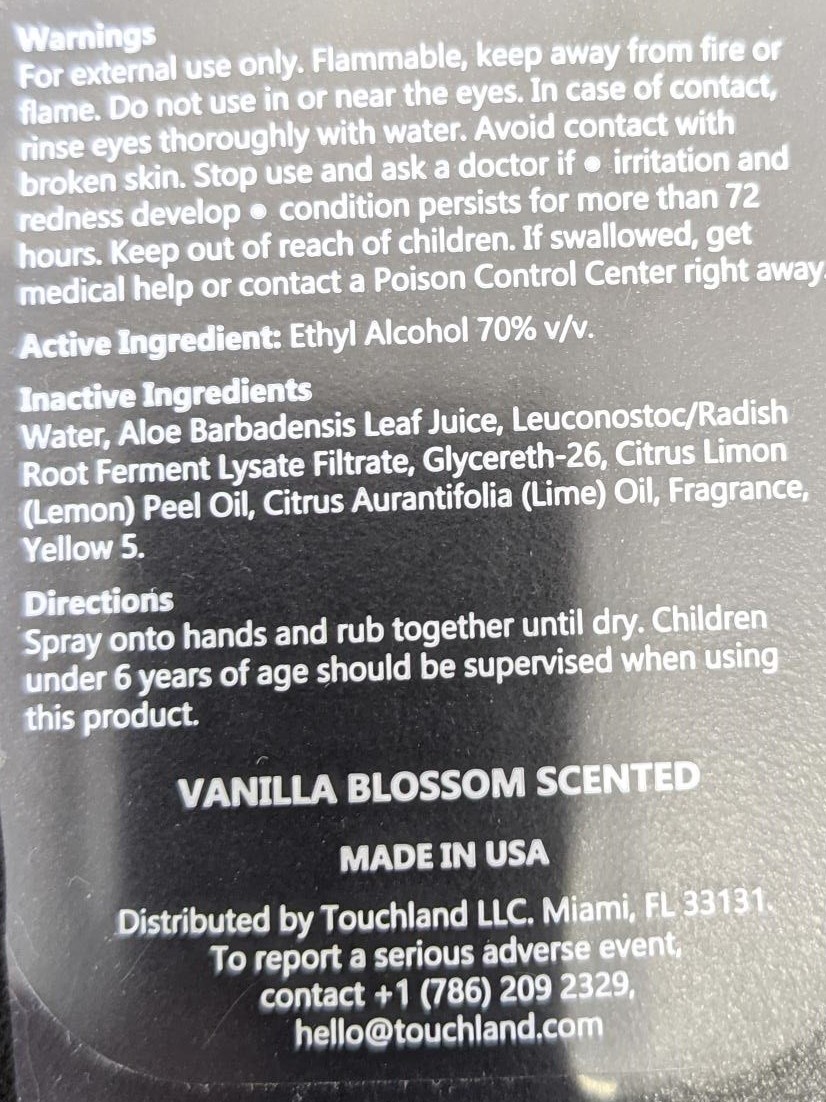 DRUG LABEL: Vanilla Blossom
NDC: 76150-283 | Form: SPRAY
Manufacturer: Bell International Laboratories, Inc.
Category: otc | Type: HUMAN OTC DRUG LABEL
Date: 20210823

ACTIVE INGREDIENTS: ALCOHOL 70 mL/100 mL
INACTIVE INGREDIENTS: WATER; LEUCONOSTOC/RADISH ROOT FERMENT FILTRATE; LEMON OIL; GLYCERETH-26; ALOE VERA LEAF; LIME OIL; FD&C YELLOW NO. 5

Touchland Vanilla Blossom Hand Sanitizer Spray

Active Ingredient

Ethyl Alcohol 70% v/v

Purpose

Antiseptic

Uses

To decrease bacteria on the skin

Recommended for repeated use

Warnings

For external use only

Flammable, keep away from fire or flame

Do not use in or near the eyes. In case of contact, rinse eyes thoroughly with water. Avoid contact with broken skin

Stop use and ask a doctor if irritation and redness develop

Condition persists for more than 72 hours

Keep out of reach of children. If swallowed, get medical help or contact a Poison Control Center right away

Directions

Place enough product in your palm to thoroughly cover your hands

Children under 6 years of age should be supervised when using this product

Rub hands together briskly until dry

Inactive Ingredients

Water, Aloe Barbadensis Leaf Juice, Leuconostoc/Radish Root Ferment Lysate Filtrate, Glycereth-26, Citrus Limon (Lemon) Peel Oil, Citrus Aurantifolia (Lime) Oil, Fragrance, Yellow 5

Other Information

Protect the product in this container from excessive heat and direct sun

Store below 104F (40C)

May discolor certain fabrics